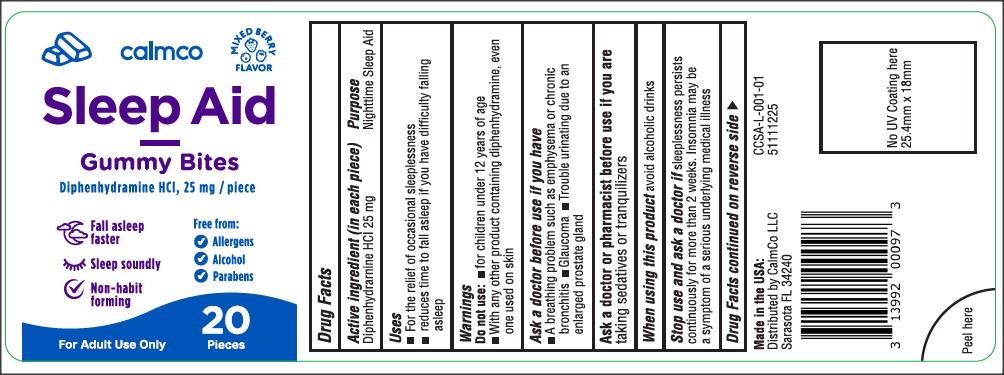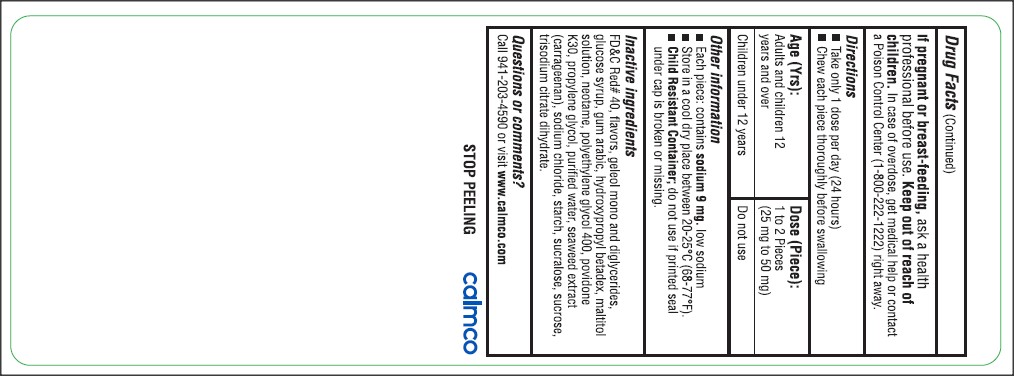 DRUG LABEL: CalmCo Sleep Aid Gummy Bite
NDC: 73282-2518 | Form: BAR, CHEWABLE
Manufacturer: CalmCo LLC
Category: otc | Type: HUMAN OTC DRUG LABEL
Date: 20241207

ACTIVE INGREDIENTS: DIPHENHYDRAMINE HYDROCHLORIDE 25 mg/1 1
INACTIVE INGREDIENTS: CARRAGEENAN; STARCH, CORN; MALTITOL; GLYCERYL MONO AND DIPALMITOSTEARATE; NEOTAME; SODIUM CHLORIDE; POVIDONE K30; SUCRALOSE; POLYETHYLENE GLYCOL 400; TRISODIUM CITRATE DIHYDRATE; PROPYLENE GLYCOL; SUCROSE; CORN SYRUP; HYDROXYPROPYL BETADEX; ACACIA; WATER; FD&C RED NO. 40

CalmCo Adult Sleep Aid Gummy Bite

Active ingredient and Purpose

Active ingredient | Purpose
Diphenhydramine HCl 25 mg .................. | Nighttime sleep aid

Warnings

Do not use

- for children under 12 years of age
- with any other product containing diphenhydramine, even one used on skin

Ask a doctor before use if you have

- a breathing problem such as emphysema or chronic bronchitis
- glaucoma
- trouble urinating due to an enlarged prostate gland

Ask a doctor or pharmacist before use if you are

taking sedatives or tranquilizers

When using this product

avoid alcoholic drinks

Stop use and ask a doctor if

sleeplessness persists continuously for more than 2 weeks. Insomnia may be a symptom of a serious underlying medical illness

If pregnant or breast-feeding

ask a health professional before use.

Keep out of reach of children

In case of overdose, get medical help or contact a Poison Control Center (1-800-222-1222) right away.

Uses

- for the relief of occasional sleeplessness
- reduces time to fall asleep if you have difficulty falling asleep

Other Information

- each piece: contains: sodium 9 mg . low sodium
- Store in a cool dry place between 20-25°C (68-77°F).
- Child Resistant Container;do not use if printed seal under cap is broken or missing.

Inactive Ingredients

FD&C Red# 40, flavors, geleol mono and diglycerides, glucose syrup, gum arabic, hydroxypropyl betadex, maltitol solution, neotame, polyethylene glycol 400, povidone K30, propylene glycol, purified water, seaweed extract (carrageenan), sodium chloride, starch, sucralose, sucrose, trisodium citrate dihydrate.

Directions

- take only 1 dose per day (24 hours)
- chew each piece thoroughly before swallowing

Age (Yrs) | Dose (per piece)
adults and children 12 years and over | 1 to 2 pieces (25 mg to 50 mg)
children under 12 years | do not use

Questions or Comments?

Call 941-203-4590 or visit www.calmco.com